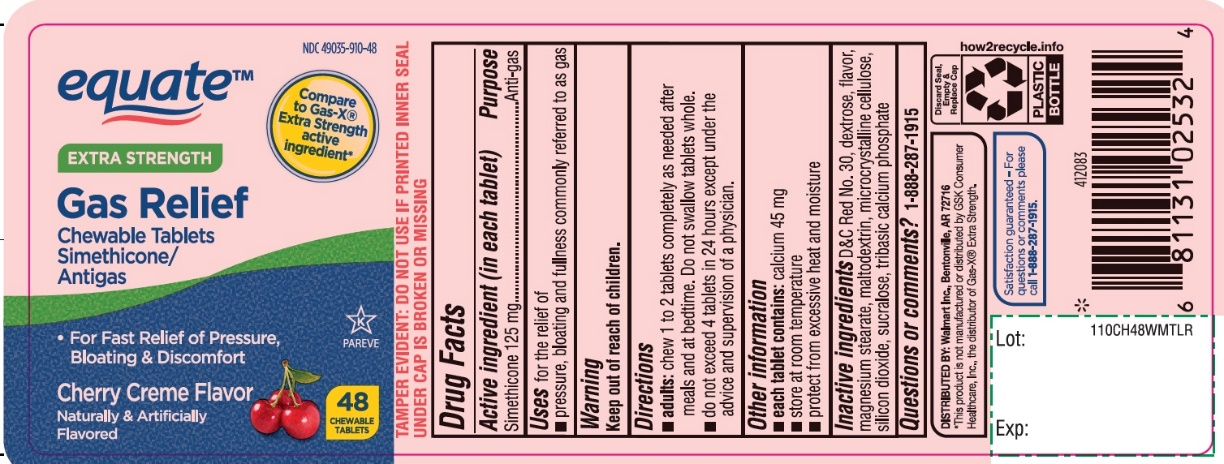 DRUG LABEL: Extra Strength Gas Relief
NDC: 49035-910 | Form: TABLET, CHEWABLE
Manufacturer: Wal-Mart Stores,Inc.,
Category: otc | Type: HUMAN OTC DRUG LABEL
Date: 20251027

ACTIVE INGREDIENTS: DIMETHICONE, UNSPECIFIED 125 mg/1 1
INACTIVE INGREDIENTS: DEXTROSE, UNSPECIFIED FORM; D&C RED NO. 30; MAGNESIUM STEARATE; MALTODEXTRIN; MICROCRYSTALLINE CELLULOSE; SILICON DIOXIDE; SUCRALOSE; TRIBASIC CALCIUM PHOSPHATE

equate Extra Strength Gas Relief 48 Chewable Tablets

Active ingredient (in each tablet)

Simethicone 125 mg

Purpose

Antigas

Uses For the relief of

- Pressure, bloating and fullness commonly referred to as gas

Directions

• adults:chew 1 or 2 tablets completely as needed after meals and at bedtime. Do not swallow tablets whole.

•do not exceed 4 tablets in 24 hour period except under the advice and supervision of a physician

Other information

- each tablet contains: calcium 45 mg
- store at room temperature
- protect from excessive heat and moisture

Inactive ingredients

D&C Red 30, dextrose, flavor, magnesium stearate, maltodextrin, microcrystalline cellulose, silicon dioxide, sucralose, tribasic calcium phosphate

Questions or comments?

1-888-287-1915

Principal Display Panel

NDC 49035-910-48

equate®

Compare toE xtra Strength Gas-X® Active Ingredient*

Extra Strength

Gas Relief

Chewable Tablets Simethicone/ Antigas

- For Fast Relief of Pressure, Bloating & Discomfort

Cherry Creme Flavor

Naturally & Artificially Flavored

48 CHEWABLE TABLETS

TAMPER EVIDENT: Do not use if printed inner seal is broken or missing

Satisfaction guaranteed-for questions or comments please call 1-888-287-1915

DISTRIBUTED BY: Walmart Inc., Bentonville, AR 72716

*This product is not manufactured or distributed by GSK Consumer Healthcare, Inc., the distributer of GAS-X® Extra Strength.